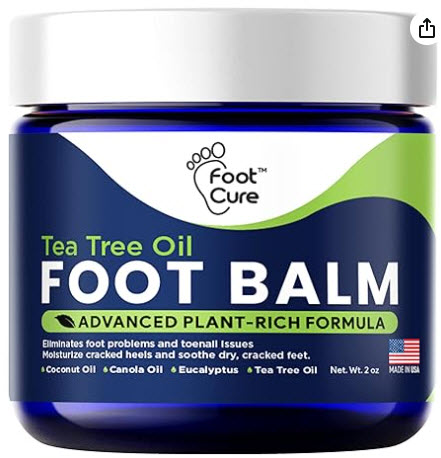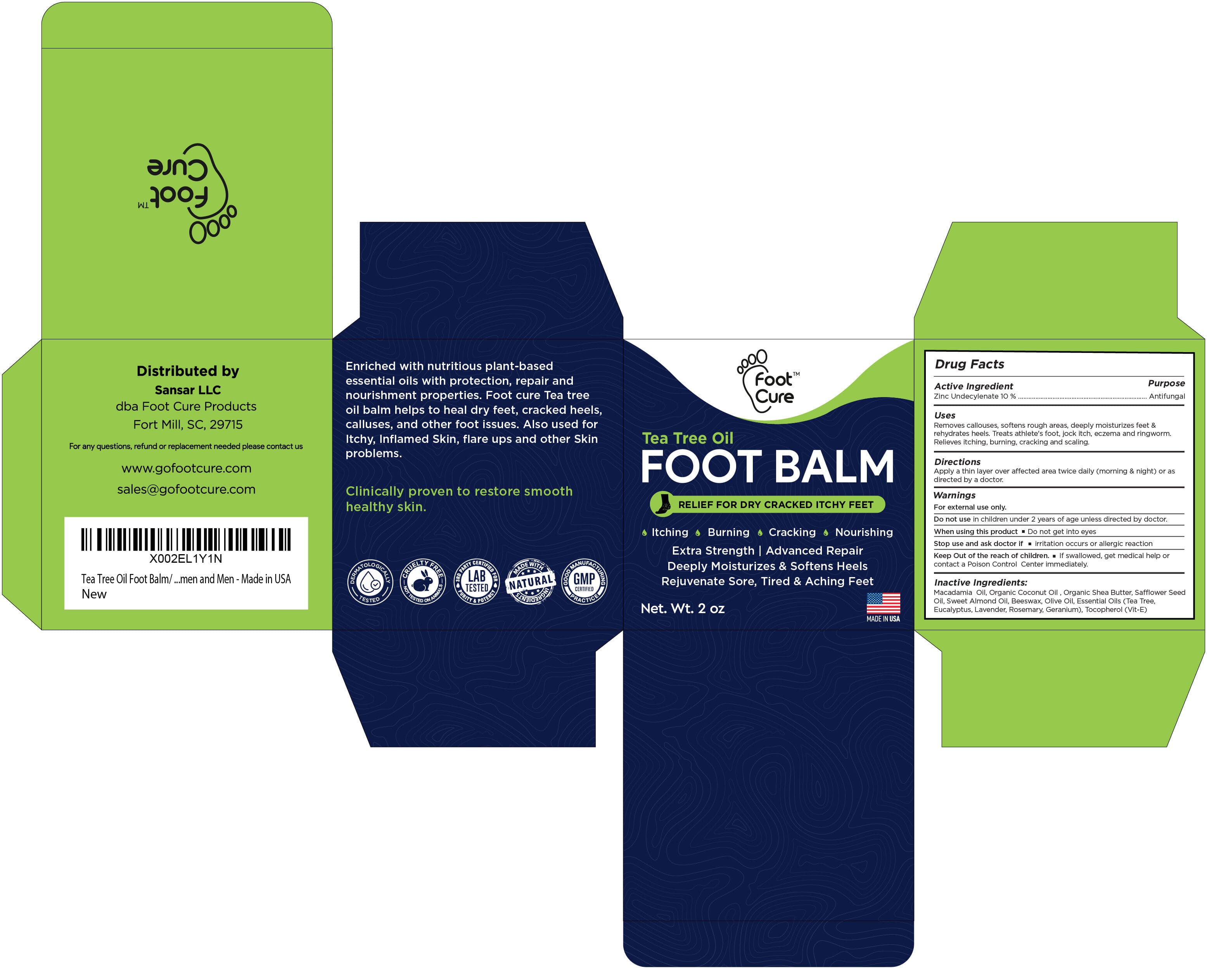 DRUG LABEL: Foot Cure Antifungal Foot Balm
NDC: 83691-001 | Form: OINTMENT
Manufacturer: Sansar LLC
Category: otc | Type: HUMAN OTC DRUG LABEL
Date: 20240722

ACTIVE INGREDIENTS: ZINC UNDECYLENATE 5.7 g/5.7 g
INACTIVE INGREDIENTS: COCONUT OIL; SYNTHETIC BEESWAX; SHEA BUTTER; MACADAMIA OIL; ALPHA-TOCOPHEROL; SAFFLOWER OIL; OLIVE OIL; ROSEMARY OIL; EUCALYPTUS OIL; GERANIUM OIL, ALGERIAN TYPE; ALMOND OIL; TEA TREE OIL; LAVENDER OIL

Active Ingredient

Zink Undecylenate 10% -------------------------- Antifungal

Uses

Removes callouses, softens rough areas, deeply moisturizes feed & rehydrates heels. Treats athlete's foot, jock itch, eczema and ringworm. Relieves itching, burning, cracking and scaling.

Warnings

For External Use only.

Directions

Apply a thin layer over affected area twice daily (morning & night) or as directed by a doctor.

Inactive Ingredients

Macadamica Oil, Organic Coconut Oil, Organic Shea Butter, Safflower Seed Oil, Sweet Almond Oil, Beeswax, Olive Oil, Essential Oils (Tea Tree, Eucalyptus, Lavender, Rosemary, Geranium), Tocopherol (Vit-E)

DOSAGE AND ADMINISTRATION

2 Ounce

INDICATIONS AND USAGE

Apply a thin layer over affected area twice daily (morning and night) or as directed by a doctor.

Keep out of reach of children.

Do not use in children under 2 years of age unless directed by doctor.

PURPOSE

Relief for Dry Cracked Itchy Feet